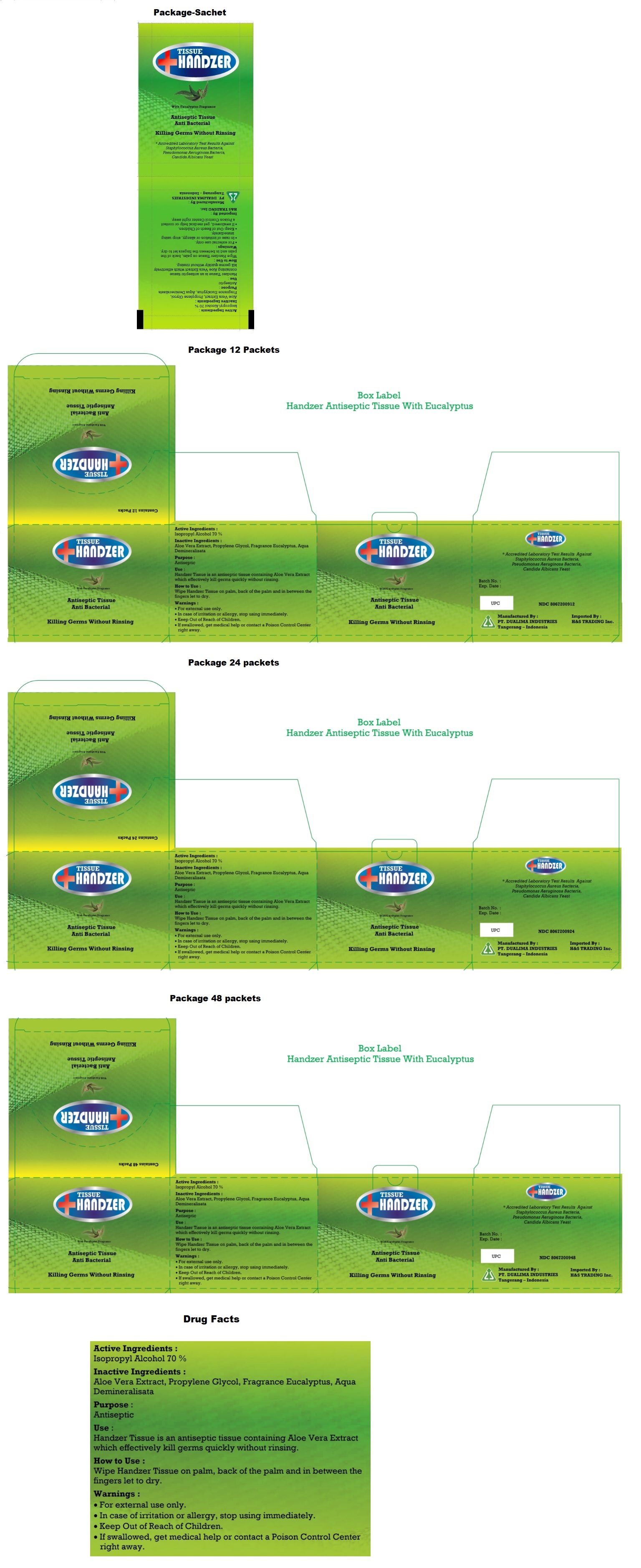 DRUG LABEL: TISSUE HANDZER
NDC: 80672-009 | Form: CLOTH
Manufacturer: PT. DUALIMA INDUSTRIES
Category: otc | Type: HUMAN OTC DRUG LABEL
Date: 20201008

ACTIVE INGREDIENTS: ISOPROPYL ALCOHOL 70 mL/100 mL
INACTIVE INGREDIENTS: ALOE VERA LEAF; PROPYLENE GLYCOL; FRAGRANCE EUCALYPTUS SPEARMINT ORC1601627; WATER

TISSUE HANDZER Antiseptic Tissue

Active Ingredients :

Isopropyl Alcohol 70%

Purpose :

Antiseptic

Use :

Handzer Tissue is an antiseptic tissue containing Aloe Vera Extract which effectively kill germs quickly without rinsing.

Warnings :

• For external use only.

• In case of irritation or allergy, stop using immediately.

- Keep Out of Reach of Children.
- If swallowed, get medical help or contact a Poison Control Center right away.

How to Use :

Wipe Handzer Tissue on palm, back of the palm and in between the fingers let to dry.

Inactive Ingredients :

Aloe Vera Extract, Propylene Glycol, Fragrance Eucalyptus, Aqua Demineralisata

With Eucalyptus Fragrance

Anti Bacterial

Killing Germs Without Rinsing

*Accredited Laboratory Test Results Against Staphylococcus Aureus Bacteria, Pseudomonas Aeruginosa Bacteria, Candida Albicans Yeast

Imported By :

H&S TRADING Inc.

Manufactured By :

PT. DUALIMA INDUSTRIES

Tangerang - Indonesia